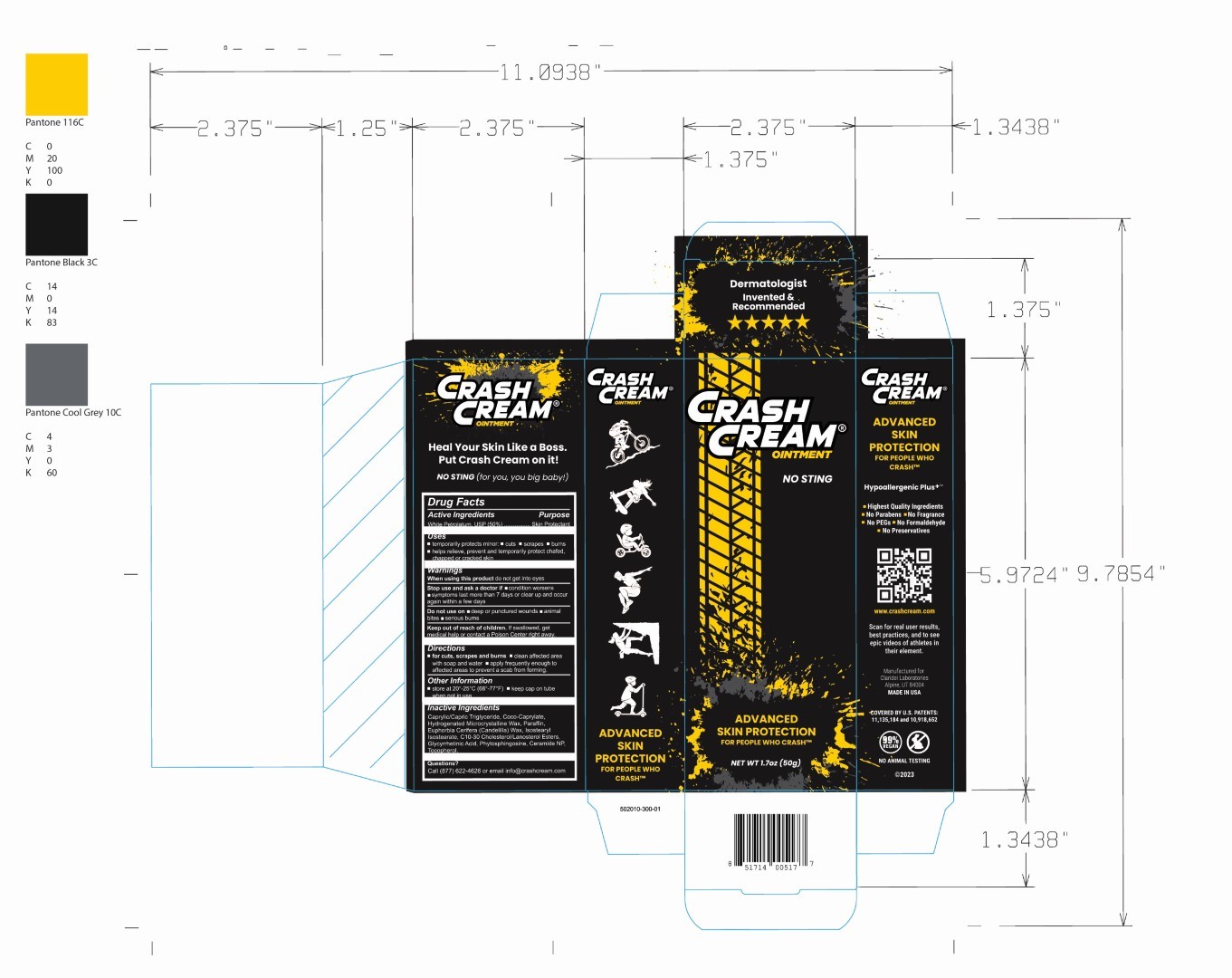 DRUG LABEL: Crash Cream
NDC: 61387-251 | Form: OINTMENT
Manufacturer: Claridei Laboratories
Category: otc | Type: HUMAN OTC DRUG LABEL
Date: 20251215

ACTIVE INGREDIENTS: WHITE PETROLATUM 50 g/100 g
INACTIVE INGREDIENTS: CANDELILLA WAX; MICROCRYSTALLINE WAX; MEDIUM-CHAIN TRIGLYCERIDES; ISOSTEARYL ISOSTEARATE; ENOXOLONE; TOCOPHEROL; C10-30 CHOLESTEROL/LANOSTEROL ESTERS; CERAMIDE NP; COCO-CAPRYLATE; PHYTOSPHINGOSINE; PARAFFIN

Crash Cream

Active Ingredient

White Petrolatum USP (50%)

Purpose

Skin Protectant

Uses

- temporarily protects minor: cuts, scrapes, burns
- helps relieve, prevent and temporarily protect chaged, chapped or cracked skin

Keep out of reach of children. If swallowed, get medical help or contact a Poison Control Center right away

Stop use and ask a doctor if

- condition worsens
- symptoms last more than 7 days or clear up and occur again within a few days

Warnings

When using this product do not get into eyes

Do not use on

- deep or punctured wounds
- animal bites
- serious burns

Directions

- for cuts, scrapes, and bums
- Clean affected area with soap and water
- apply frequently enoughto infected areas to prevent a scab from forming

Inactive ingredients

Caprylic/Capric Triglyceride, Coco-Caprylate, Hydrogenated Microcrystalline Wax, Paraffin, Euphorbia Cerifera (Candelilla) Wax, Isostearyl Isostearate, C10-30 Cholersterol/Lanosterol Esters, Glycyrhetinic Acid, Phytosphingosine, Ceramide NP, Tocopherol

PACKAGE LABEL

Crash Cream Ointment

No Sting

Advanced Skin Protection

Net Wt 1.7oz (50g)